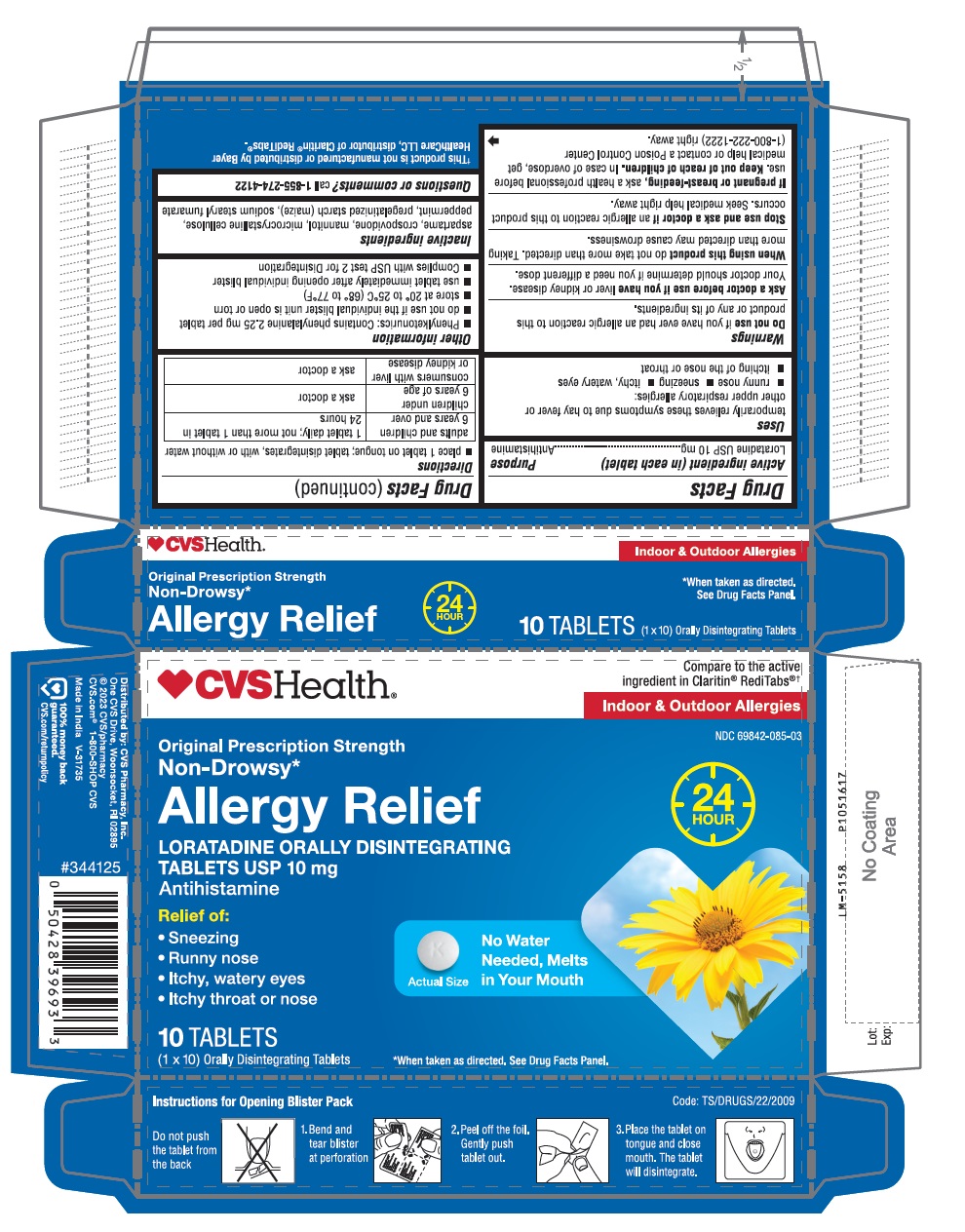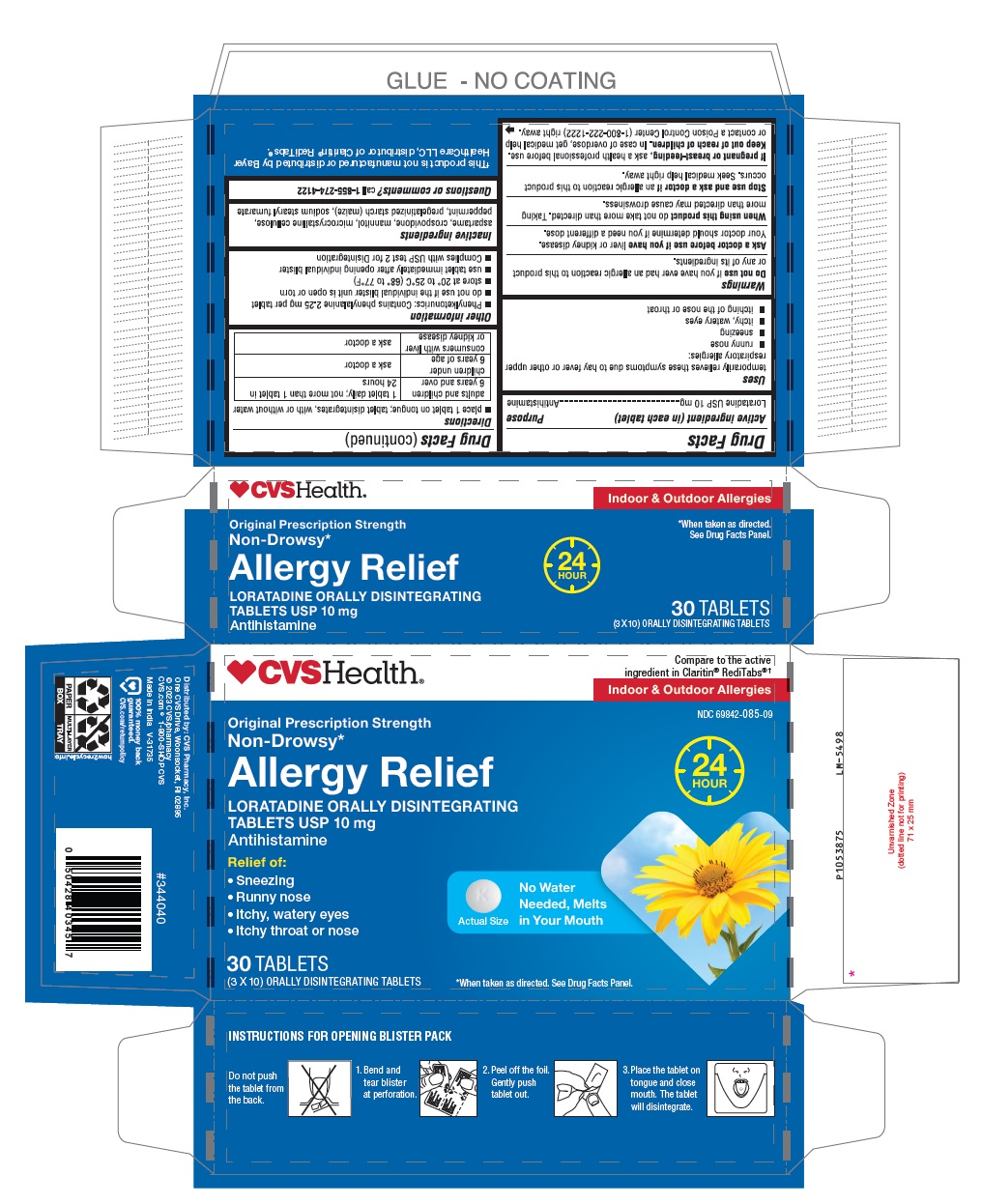 DRUG LABEL: Loratadine ODT
NDC: 69842-085 | Form: TABLET, ORALLY DISINTEGRATING
Manufacturer: CVS Pharmacy, Inc.
Category: otc | Type: Human OTC Drug Label
Date: 20250317

ACTIVE INGREDIENTS: LORATADINE 10 mg/1 1
INACTIVE INGREDIENTS: ASPARTAME; CROSPOVIDONE (120 .MU.M); MANNITOL; MICROCRYSTALLINE CELLULOSE; PEPPERMINT; STARCH, CORN; SODIUM STEARYL FUMARATE

Loratadine Orally Disintegrating Tablets USP 10 mg

Active ingredient (in each tablet)

Loratadine USP 10 mg

Purpose

Antihistamine

Uses

temporarily relieves these symptoms due to hay fever or other upper respiratory allergies:

- runny nose
- sneezing
- itchy, watery eyes
- itching of the nose or throat

Do not use

if you have ever had an allergic reaction to this product or any of its ingredients.

Ask a doctor before use if you have

liver or kidney disease. Your doctor should determine if you need a different dose.

When using this product

do not take more than directed. Taking more than directed may cause drowsiness.

Stop use and ask a doctor if

an allergic reaction to this product occurs. Seek medical help right away.

If pregnant or breast-feeding,

ask a health professional before use.

Keep out of reach of children.

In case of overdose, get medical help or contact a Poison Control Center (1-800-222-1222) right away.

Directions

- place 1 tablet on tongue; tablet disintegrates, with or without water

adults and children 6 years and over | 1 tablet daily; not more than 1 tablet in 24 hours
children under 6 years of age | ask a doctor
consumers with liver or kidney disease | ask a doctor

Other information

- Phenylketonurics: Contains phenylalanine 2.25 mg per tablet
- do not use if the individual blister unit is open or torn
- store at 20° to 25°C (68° to 77°F)
- use tablet immediately after opening individual blister
- Complies with USP test 2 for Disintegration

Inactive ingredients

aspartame, crospovidone, mannitol, microcrystalline cellulose, peppermint, pregelatinized starch (maize), sodium stearyl fumarate

Questions or comments?

call 1-855-274-4122
Distributed by: CVS Pharmacy, Inc.

one CVS Drive, Woonsocket, Rl 02895

© 2023 CVS/pharmacy
CVS.com® 1-800-SHOP CVS

Made in India

V-31735
100% money back guaranteed.
CVS.com/returnpolicy

PACKAGE LABEL-PRINCIPAL DISPLAY PANEL - 10 mg, Blister Carton 10 (1 X 10) Orally Disintegrating Tablets

♥CVS Health®
Compare to the active

ingredient in Claritin® RediTabs®†

Indoor &Outdoor Allergies
NDC 69842-085-03
Original Prescription Strength
Non-Drowsy*
Allergy Relief
LORATADINE ORALLY DISINTEGRATING
TABLETS USP 10 mg
Antihistamine
24

HOUR
Relief of:

- Sneezing
- Runny nose
- Itchy, watery eyes
- Itchy throat or nose

Actual Size

No Water

Needed, Melts

in Your Mouth

10 TABLETS
(1 X 10) Orally Disintegrating Tablets

*When taken as directed. See Drug Facts Panel.

PACKAGE LABEL-PRINCIPAL DISPLAY PANEL - 10 mg, Blister Carton 30 (3 x 10) Tablets

♥CVS Health®
Compare to the active

ingredient in Claritin® RediTabs®†

Indoor &Outdoor Allergies
NDC 69842-085-09
Original Prescription Strength
Non-Drowsy*
Allergy Relief
LORATADINE ORALLY DISINTEGRATING
TABLETS USP 10 mg
Antihistamine
24

HOUR
Relief of:

- Sneezing
- Runny nose
- Itchy, watery eyes
- Itchy throat or nose

Actual Size

No Water

Needed, Melts

in Your Mouth

30 TABLETS
(3 X 10) ORALLY DISINTEGRATING TABLETS

*When taken as directed. See Drug Facts Panel.